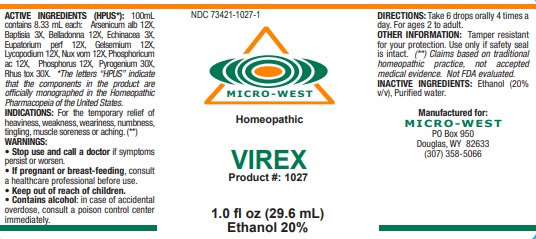 DRUG LABEL: VIREX
NDC: 73421-1027 | Form: LIQUID
Manufacturer: White Manufacturing Inc. DBA Micro-West
Category: homeopathic | Type: HUMAN OTC DRUG LABEL
Date: 20221202

ACTIVE INGREDIENTS: ARSENIC TRIOXIDE 12 [hp_X]/29.6 mL; BAPTISIA TINCTORIA ROOT 3 [hp_X]/29.6 mL; ATROPA BELLADONNA 12 [hp_X]/29.6 mL; ECHINACEA ANGUSTIFOLIA WHOLE 3 [hp_X]/29.6 mL; EUPATORIUM PERFOLIATUM FLOWERING TOP 12 [hp_X]/29.6 mL; GELSEMIUM SEMPERVIRENS ROOT 12 [hp_X]/29.6 mL; LYCOPODIUM CLAVATUM SPORE 12 [hp_X]/29.6 mL; STRYCHNOS NUX-VOMICA SEED 12 [hp_X]/29.6 mL; PHOSPHORIC ACID 12 [hp_X]/29.6 mL; PHOSPHORUS 12 [hp_X]/29.6 mL; RANCID BEEF 30 [hp_X]/29.6 mL; TOXICODENDRON PUBESCENS LEAF 30 [hp_X]/29.6 mL
INACTIVE INGREDIENTS: ALCOHOL; WATER

VIREX

ACTIVE INGREDIENT

ACTIVE INGREDIENTS (HPUS*): 100mL contains 8.33 mL each: Arsenicum alb 12X, Baptisia 3X, Belladonna 12X, Echinacea 3X,
Eupatorium perf 12X, Gelsemium 12X, Lycopodium 12X, Nux vom 12X, Phosphoricum ac 12X, Phosphorus 12X, Pyrogenium 30X,
Rhus tox 30X.

*The letters “HPUS” indicate that the components in the product are officially monographed in the Homeopathic Pharmacopeia of the United States.

(**) Claims based on traditional homeopathic practice, not accepted medical evidence. Not FDA evaluated

INDICATIONS AND USAGE

INDICATIONS: For the temporary relief of heaviness, weakness, weariness, numbness, tingling, muscle soreness or aching. (**)

WARNINGS:
• Stop use and call a doctor if symptoms persist or worsen.
• If pregnant or breast-feeding, consult a healthcare professional before use.
• Keep out of reach of children.
• Contains alcohol: in case of accidental overdose, consult a poison control center immediately.

• Keep out of reach of children.

DOSAGE AND ADMINISTRATION

DIRECTIONS: Take 6 drops orally 4 times a day. For ages 2 to adult.

OTHER INFORMATION: Tamper resistant for your protection. Use only if safety seal is intact.

INACTIVE INGREDIENTS: Ethanol (20% v/v), Purified water.

QUESTIONS

Manufactured for:
MICRO-WEST
PO Box 950
Douglas, WY 82633
(307) 358-5066

PACKAGE LABEL

NDC 73421-1027-1

MICRO-WEST

Homeopathic

VIREX

Product #: 1027

1.0 fl oz (29.6 mL)

Ethanol 20%

PURPOSE

For the temporary relief of heaviness, weakness, weariness, numbness, tingling, muscle soreness or aching